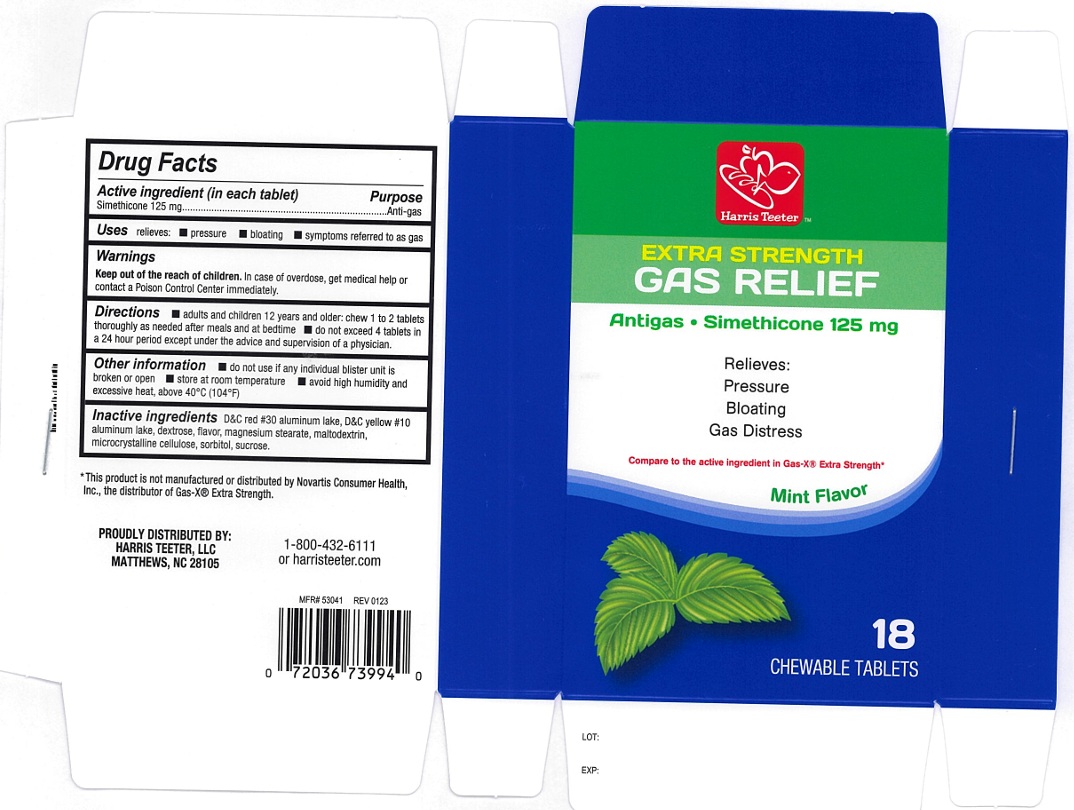 DRUG LABEL: Extra Strength Gas Relief
NDC: 69256-135 | Form: TABLET, CHEWABLE
Manufacturer: Harris Teeter, LLC
Category: otc | Type: Human OTC Drug Label
Date: 20250205

ACTIVE INGREDIENTS: DIMETHICONE 125 mg/1 1
INACTIVE INGREDIENTS: D&C RED NO. 30 ALUMINUM LAKE; MAGNESIUM STEARATE; CELLULOSE, MICROCRYSTALLINE; SORBITOL; SUCROSE; MALTODEXTRIN; DEXTROSE, UNSPECIFIED FORM; D&C YELLOW NO. 10 ALUMINUM LAKE

Extra Strength Gas Relief

ACTIVE INGREDIENT(in each tablet)

Simethicone 125 mg

PURPOSE

Anti-gas

USE(S)

relieves:

- pressure
- bloating
- symptoms referred to as gas

WARNINGS

.

KEEP OUT OF REACH OF CHILDREN

In case of overdose, get medical help or contact a poison control center immediately.

DIRECTIONS

- adults and children 12 years and older: chew 1 to 2 tablets thoroughly as needed after meals and at bedtime
- do not exceed 4 tablets in a 24 hour period except under the advice and supervision of a physician.

OTHER INFORMATION

- do not use if any individual blister unit is broken or open
- store at room temperature
- avoid high humidity and excessive heat, above 40ºC (104ºF)

INACTIVE INGREDIENTS

D&C red # 30 aluminum lake, D&C yellow # 10 aluminum lake, dextrose, flavor, magnesium stearate, maltodextrin, microcrystalline cellulose, sorbitol, sucrose.

PRINCIPAL DISPLAY PANEL

Harris Teeter™

NDC 69256-135-73

EXSTRA STRENGTH

GAS RELIEF

Antigas. Simethicone 125 mg

Relieves:

Pressure

Bloating

Gas Distress

Compare to the Active Ingredient in Gas-X® Extra Strength*

Mint Flavor

18 chewable tablets